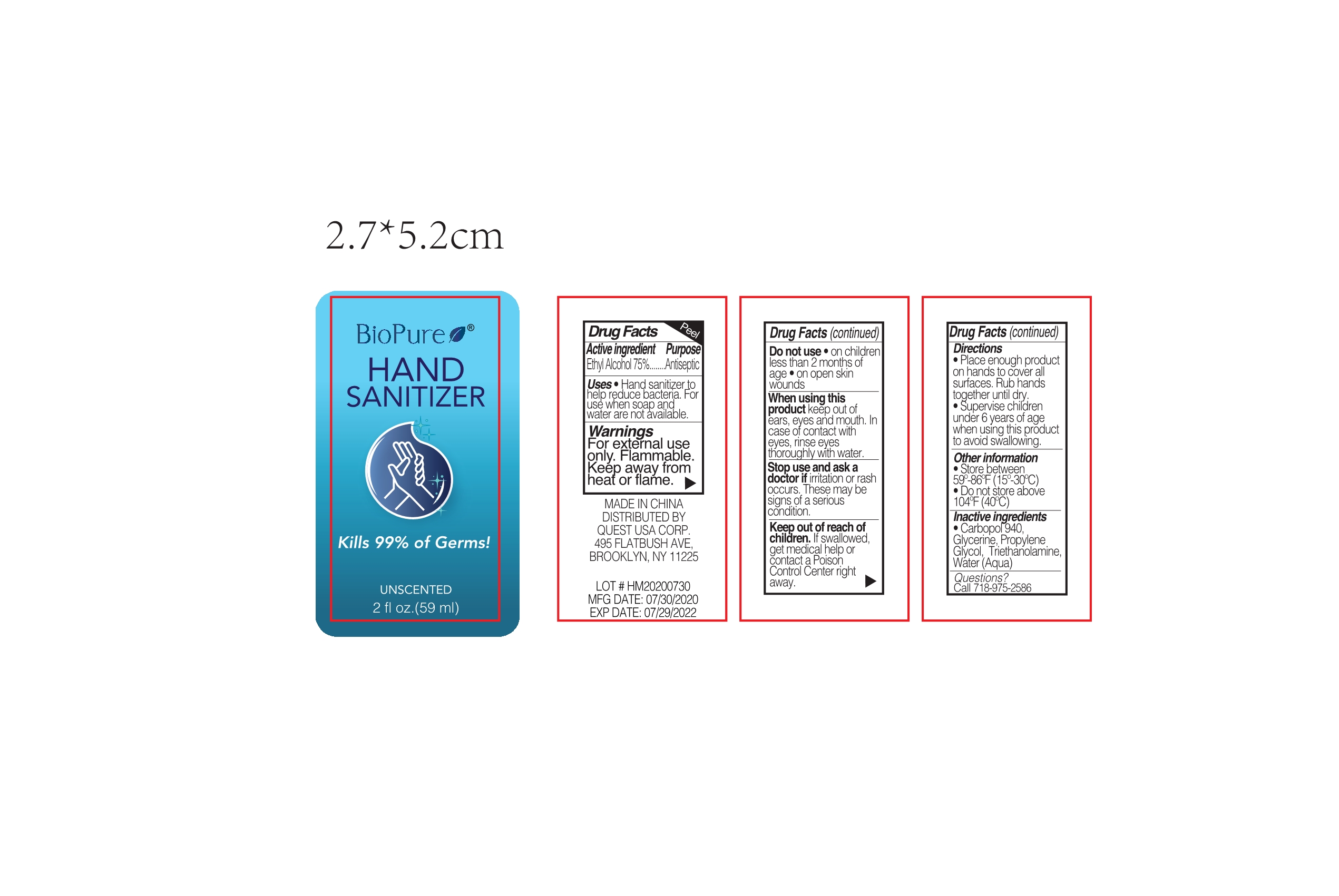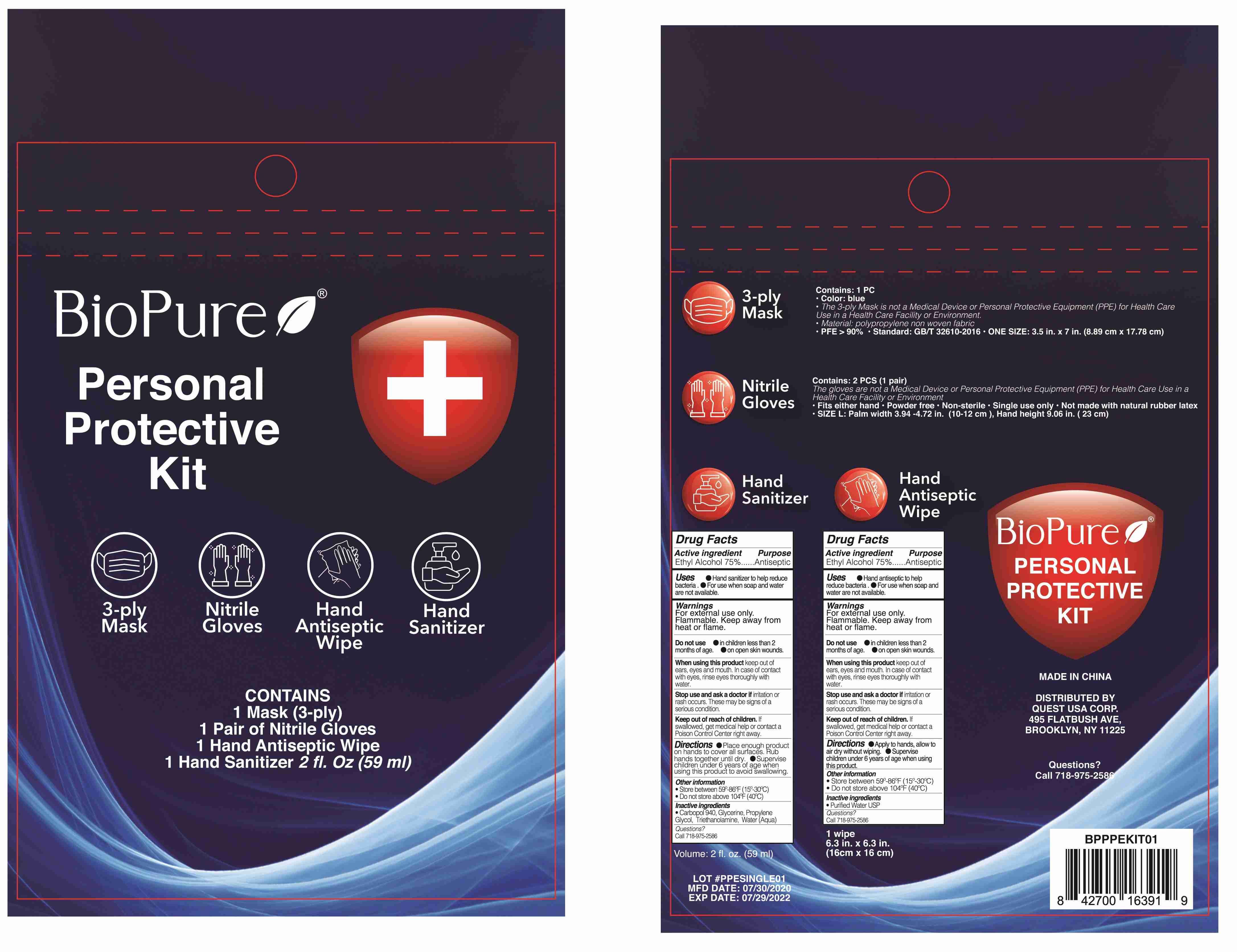 DRUG LABEL: HAND SANITIZER
NDC: 75427-013 | Form: GEL
Manufacturer: Jinhua City Wellmae Cosmetics Co., Ltd.
Category: otc | Type: HUMAN OTC DRUG LABEL
Date: 20220120

ACTIVE INGREDIENTS: ALCOHOL 75 mL/100 mL
INACTIVE INGREDIENTS: CARBOMER HOMOPOLYMER TYPE C (ALLYL PENTAERYTHRITOL CROSSLINKED); WATER; PROPYLENE GLYCOL; GLYCERIN; TROLAMINE

75427-013
HAND SANITIZER

ACTIVE INGREDIENT

Ethyl Alcohol 75%

Purpose

Antiseptic

Uses

●Hand sanitizer to help reduce bacteria.
●For use when soap and water are not available

WARNINGS

For External Use Only. Flammable. Keep Away From Heat Or Flame.

Do not use

●on children less than 2 months of age.
●on open skin wounds.

When using this product

keep out of ears, eyes and mouth. In case of contact with eyes, rinse eyes thoroughly with water.

Stop use and ask a doctor

if irritation or rash occurs. These may be signs of a serious condition.

Keep out of reach of children

If swallowed, get medical help or contact a Poison Control Center right away.

Directions

Place enough product on hands to cover all surfaces. Rub hands together until dry.

Supervise children under 6 years of age when using this product to avoid swallowing

Other Information

Store between 59°-86°F (15°-30℃)

Do not store above 104°F (40℃)

Inactive Ingredients

Carbopol 940, Glycerine, Propylene GlycoL, Triethanolamine, Water (Aqua)